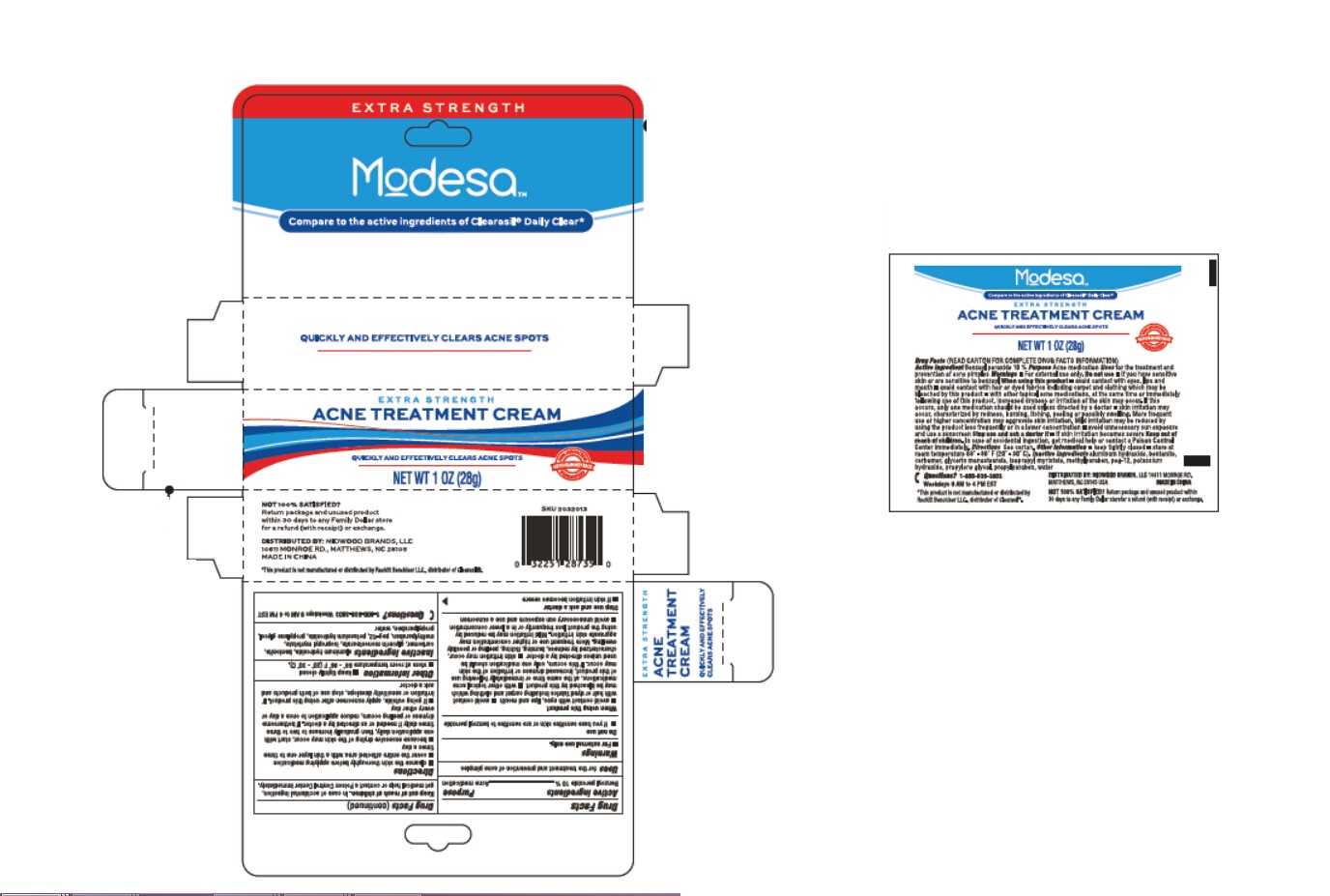 DRUG LABEL: 
                  Modesa
                        
                  

NDC: 55621-017 | Form: CREAM
Manufacturer: Zhejiang Jingwei Pharmaceutic Al Co., Ltd.
Category: otc | Type: HUMAN OTC DRUG LABEL
Date: 20231027

ACTIVE INGREDIENTS: BENZOYL PEROXIDE 10 g/100 g
INACTIVE INGREDIENTS: ALUMINUM HYDROXIDE; BENTONITE; CARBOMER 940; DIGLYCERIN MONOSTEARATE; METHYLPARABEN; POLYETHYLENE GLYCOL 600; POTASSIUM HYDROXIDE; PROPYLENE GLYCOL; PROPYLPARABEN; WATER

Active ingredients

Benzoyl peroxide 10%

Purpose

Acne medication

INDICATIONS AND USAGE

for the treatment and prevention of acne pimples Uses

Warnings

•For external use only

Do not use

•if you have sensitive skin or are sensitive to benzoyl peroxide

When using this product

•avoid contact with eyes, lips and mouth •avoid contact

with hair or dyed fabrics including carpet and clothing which

may be bleached by this product •with other topical acne

medicaitons, at the same time nor immediately following use

of this product, increased dryness or irritation of the skin

may occur. If this occurs, only one medicaiton should be used

unless directed by a doctor •skin irritaiton may occur,

characterized by redness, burning, itching, peeling or possibly

swelling. More frequent use or higher concentration may

aggravtae skin irritation. Mild irritation may be reduced by

using the product less frequently or in a lower concentration

•avoid unnecessary sun exposure and use a sunscreen

Stop use and ask a doctor

•if skin irritation becomes severe

KEEP OUT OF REACH OF CHILDREN

In case of accidental ingestion, Keep out of reach of children.

get medical help or contact a Poison Control Center immediately.

Directions

•cleanse the skin thoroughly before applying medication

•cover the entire affected area with a thin layer one to three

times a day

•because excessive drying of the skin may occur, start with

one applicaiton daily, then gradually increase to two to three

times daily if needed or as directed by a doctor. If bothersome

dryness or peeling occurs, reduce application to once a day or

every other day

•if going outside, apply sunscreen after using this product. If

irritation or sensitivity develops, stop use of both products and

ask a doctor

STORAGE AND HANDLING

•keep tightly closed Other information

•store at room temperature 68° - 86° F (20° - 30°C).

aluminum hydroxide, bentonite, Inactive ingredients

carbomer, glycerin monostearate, isopropyl myristate,

methylparaben, peg-12, potassium hydroxide, propylene glycol,

propylparaben, water

QUESTIONS

1-800-639-3803 Weekdays 9 AM to 4 PM EST Questions?